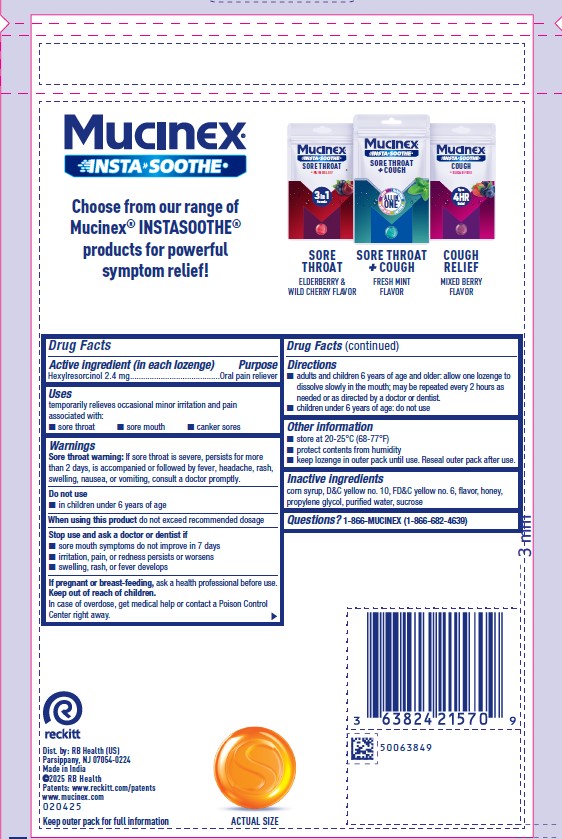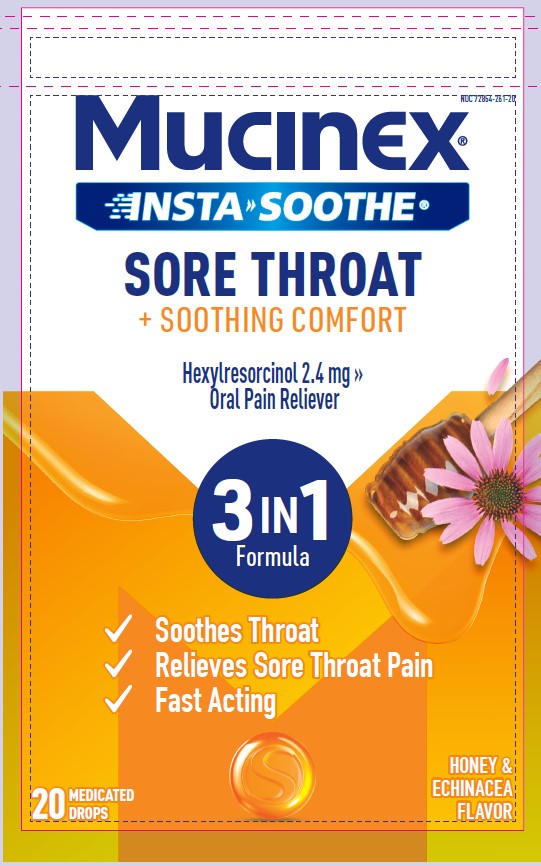 DRUG LABEL: MUCINEX INSTASOOTHE
NDC: 72854-261 | Form: LOZENGE
Manufacturer: RB Health (US) LLC
Category: otc | Type: HUMAN OTC DRUG LABEL
Date: 20250408

ACTIVE INGREDIENTS: HEXYLRESORCINOL 2.4 mg/1 1
INACTIVE INGREDIENTS: CORN SYRUP; D&C YELLOW NO. 10; FD&C YELLOW NO. 6; HONEY; PROPYLENE GLYCOL; SUCROSE; WATER

MUCINEX® INSTASOOTHE™
SORE THROAT PLUS SOOTHING COMFORT

Drug Facts

Active ingredient (in each lozenge)

Hexylresorcinol 2.4 mg

Purpose

Oral pain reliever

Uses

temporarily relieves occasional minor irritation and pain associated with

- sore throat
- sore mouth
- canker sores

Warnings

Sore throat warning

If sore throat is severe, persists for more than 2 days, is accompanied or followed by fever, headache, rash, swelling, nausea, or vomiting, consult a doctor promptly.

Do not use

- in children under 6 years of age

When using this productdo not exceed recommended dosage

Stop use and ask a doctor or dentist if

- sore mouth symptoms do not improve in 7 days
- irritation, pain, or redness persists or worsens
- swelling, rash, or fever develops

PREGNANCY OR BREAST FEEDING

If pregnant or breast-feeding,ask a health professional before use.

Keep out of reach of children.In case of overdose, get medical help or contact a Poison Control Center right away.

Directions

- adults and children 6 years of age and older: allow one lozenge to dissolve slowly in the mouth; may be repeated every 2 hours as needed or directed by a doctor or dentist.
- children under 6 years of age: do not use

Other information

- store at 20-25°C (68-77°F)
- protect contents from humidity
- Keep lozenge in outer pack until use. Reseal outer pack after use.

Inactive ingredients

corn syrup, D&C yellow no. 10, FD&C yellow no. 6, flavor, honey, propylene glycol, purified water, sucrose

Questions?

1-866-MUCINEX (1-866-682-4639)

Dist. by: RB Health (US)
Parsippany, NJ 07054-0224
Made in India

PRINCIPAL DISPLAY PANEL - 2.4 mg Pouch Bag

NDC 72854-261-20

Mucinex®
INSTASOOTHE™

SORE THROAT
+ SOOTHING COMFORT
Hexylresorcinol 2.4 mg | Oral Pain Reliever

3IN1 FORMULA

- Soothes Throat
- Relieves Sore Throat Pain
- Fast Acting

See back
panel for
actual size

HONEY &
ECHINACEA FLAVOR

20 MEDICATED DROPS